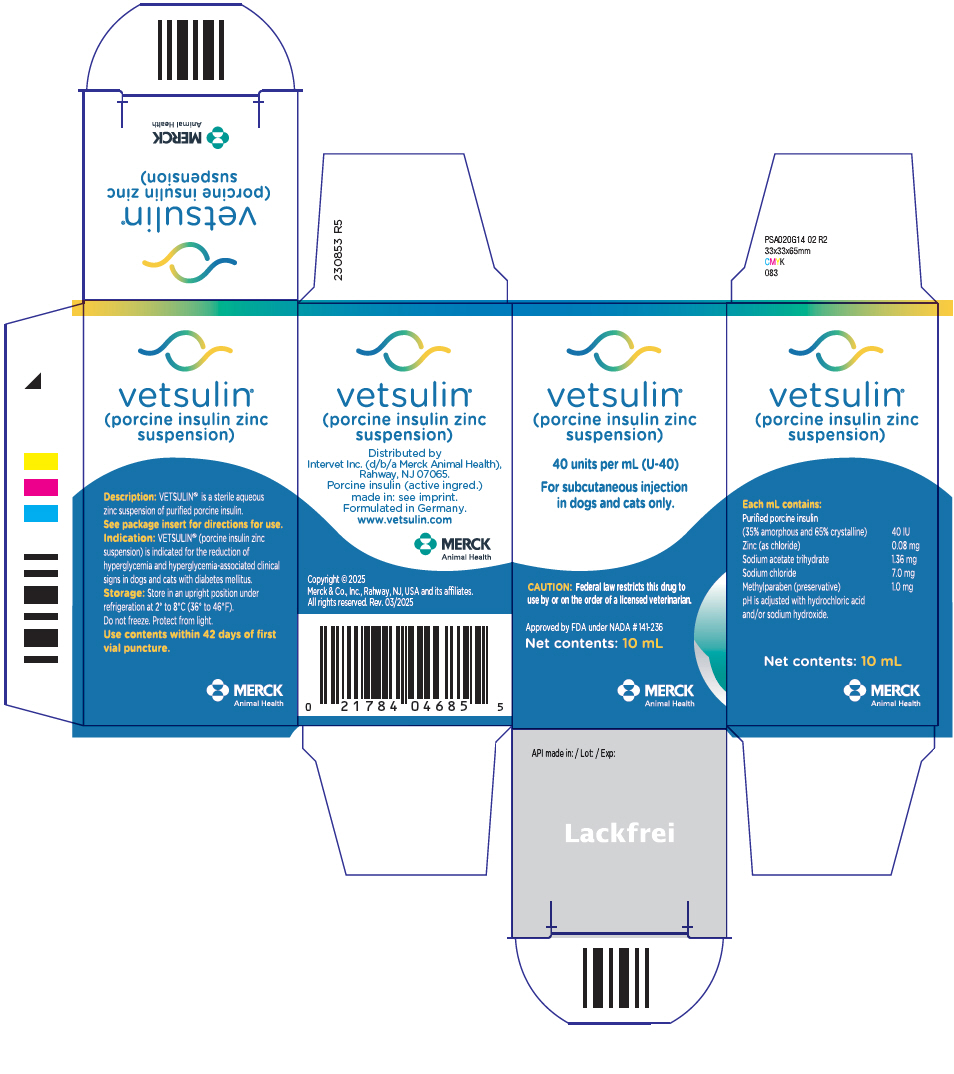 DRUG LABEL: Vetsulin
NDC: 57926-490 | Form: INJECTION
Manufacturer: Merck Sharp & Dohme Corp.
Category: animal | Type: PRESCRIPTION ANIMAL DRUG LABEL
Date: 20250630

ACTIVE INGREDIENTS: INSULIN PORK 40 [iU]/1 mL

vetsulin®
(porcine insulin zinc suspension)

Approved by FDA under NADA # 141-236

CAUTION

Federal law restricts this drug to use by or on the order of a licensed veterinarian.

DESCRIPTION

vetsulin® is a sterile aqueous zinc suspension of purified porcine insulin.

Each mL contains: | Purified porcine insulin 40 IU (35% amorphous and 65% crystalline) Zinc (as chloride) 0.08 mg Sodium acetate trihydrate 1.36 mg Sodium chloride 7.0 mg Methylparaben (preservative) 1.0 mg pH is adjusted with hydrochloric acid and/or sodium hydroxide.

INDICATION

vetsulin® (porcine insulin zinc suspension) is indicated for the reduction of hyperglycemia and hyperglycemia-associated clinical signs in dogs and cats with diabetes mellitus.

DOSAGE AND ADMINISTRATION

FOR SUBCUTANEOUS INJECTION IN DOGS AND CATS ONLY

Vials: USE OF A SYRINGE OTHER THAN A U-40 SYRINGE WILL RESULT IN INCORRECT DOSING.

Shake the vial thoroughly until a homogeneous, uniformly milky suspension is obtained. Foam on the surface of the suspension formed during shaking should be allowed to disperse before the product is used and, if required, the product should be gently mixed to maintain a homogeneous, uniformly milky suspension before use. Clumps or white particles can form in insulin suspensions: do not use the product if visible clumps or white particles persist after shaking thoroughly.

Cartridges: VETSULIN® CARTRIDGES SHOULD BE USED EXCLUSIVELY WITH VETPEN® AND 29G/12 MM PEN NEEDLES. Prior to loading vetsulin® cartridges, shake the cartridge until a homogeneous, uniformly milky suspension is obtained. Clumps or white particles can form in insulin suspensions: do not use the product if visible clumps or white particles persist after shaking. The detailed instructions for use provided with VetPen® should be strictly followed.

The injection should be administered subcutaneously, 2 to 5 cm (3/4 to 2 in) from the dorsal midline, varying from behind the scapulae to the mid-lumbar region and alternating sides.

Always provide the Owner Information Sheet with each prescription.

Dogs

The initial recommended vetsulin® dose is 0.5 IU insulin/kg body weight. Initially, this dose should be given once daily concurrently with, or right after a meal.

Twice daily therapy should be initiated if the duration of insulin action is determined to be inadequate. If twice daily treatment is initiated, the two doses should each be 25% less than the once daily dose required to attain an acceptable nadir. For example, if a dog receiving 20 units of vetsulin® once daily has an acceptable nadir but inadequate duration of activity, the vetsulin® dose should be changed to 15 units twice daily.

The veterinarian should re-evaluate the dog at appropriate intervals and adjust the dose based on clinical signs, urinalysis results, and glucose curve values until adequate glycemic control has been attained. Further adjustments in dosage may be necessary with changes in the dog's diet, body weight, or concomitant medication, or if the dog develops concurrent infection, inflammation, neoplasia, or an additional endocrine or other medical disorder.

Cats

The initial recommended dose in cats is 1 to 2 IU per injection. The injections should be given twice daily at approximately 12 hour intervals. For cats fed twice daily, the injections should be given concurrently with, or right after each meal. For cats fed ad libitum, no change in feeding schedule is needed.

The veterinarian should re-evaluate the cat at appropriate intervals and adjust the dose based on clinical signs, urinalysis results, and glucose curve values until adequate glycemic control has been attained. Further adjustments in dosage may be necessary with changes in the cat's diet, body weight, or concomitant medication, or if the cat develops concurrent infection, inflammation, neoplasia, or an additional endocrine or other medical disorder.

CONTRAINDICATIONS

Dogs and cats known to have a systemic allergy to pork or pork products should not be treated with vetsulin®. vetsulin® is contraindicated during periods of hypoglycemia.

WARNINGS

USER SAFETY WARNINGS

User Safety: For use in animals only. Keep out of the reach of children. Avoid contact with eyes. In case of contact, immediately flush eyes with copious amounts of water for 15 minutes. Accidental injection may cause clinical hypoglycemia. In case of accidental injection, seek medical attention immediately. Exposure to product may induce a local or systemic allergic reaction in sensitized individuals.

Animal Safety: Owners should be advised to observe for signs of hypoglycemia (see Owner Information Sheet). Use of this product, even at established doses, has been associated with hypoglycemia. An animal with signs of hypoglycemia should be treated immediately. Glucose should be given orally or intravenously as dictated by clinical signs. Insulin should be temporarily withheld and, subsequently, the dosage should be adjusted, if indicated. Any change in insulin should be made cautiously and only under a veterinarian's supervision. Changes in insulin strength, manufacturer, type, species (animal, human) or method of manufacture (rDNA versus animal-source insulin) may result in the need for a change in dosage.

Appropriate diagnostic tests should be performed to rule out endocrinopathies in pets that are difficult to regulate (e.g., hyperadrenocorticism in dogs and hyperthyroidism in cats).

PRECAUTIONS

Animals presenting with severe ketoacidosis, anorexia, lethargy, and/or vomiting should be stabilized with short-acting insulin and appropriate supportive therapy until their condition is stabilized. As with all insulin products, careful patient monitoring for hypoglycemia and hyperglycemia are essential to attain and maintain adequate glycemic control and prevent associated complications. Overdosage can result in profound hypoglycemia and death. Progestogens, certain endocrinopathies, and glucocorticoids can have an antagonistic effect on insulin activity. Intact bitches should be ovariohysterectomized.

Progestogen and glucocorticoid use should be avoided.

Drug Interactions:

In the US clinical effectiveness studies, dogs and cats received various medications while being treated with vetsulin® including antimicrobials, antivirals, antifungals, antihistamines, analgesics, anesthetics/tranquilizers, diuretics, bronchodilators, corticosteroids (cats), NSAIDs, thyroid hormone supplementation, hyperthyroid medication (methimazole), internal and external parasiticides, anti-emetics, dermatological topical treatments and oral supplements, ophthalmic preparations containing antimicrobials and antiinflammatories, and various vaccines. No medication interactions were reported. This drug was not studied in dogs receiving corticosteroids.

Reproductive Safety: The safety and effectiveness of vetsulin® in breeding, pregnant, and lactating dogs and cats has not been evaluated.

Use in puppies and kittens: The safety and effectiveness of vetsulin® in puppies and kittens has not been evaluated.

ADVERSE REACTIONS

Dogs

In the field effectiveness and safety study, 66 dogs were treated with vetsulin®. Sixty-two dogs were included in the assessment of safety. Hypoglycemia (defined as blood glucose < 50 mg/dL) with or without associated clinical signs occurred in 35.5% (22/62) of the dogs at various times during the study. Clinical signs of hypoglycemia were generally mild in nature (described as weakness, lethargy, stumbling, falling down, and/or depression). Disorientation and collapse were reported less frequently and occurred in 16.1% (10/62) of the dogs. Two dogs had a seizure and one dog died during the seizure. Although never confirmed, the presumptive diagnosis was hypoglycemia-induced seizures. In the rest of the dogs, hypoglycemia resolved with appropriate therapy and adjustments in insulin dosage. Seven owners recorded the following observations about the injection site on the home monitoring forms: swollen, painful, sore, and a bleb under the skin.

The following clinical observations occurred in the field study following treatment with vetsulin® and may be directly attributed to the drug or may be secondary to the diabetic state or other underlying conditions in the dogs: hematuria, vomiting, diarrhea, pancreatitis, non-specific hepatopathy/pancreatitis, development of cataracts, and urinary tract infections.

In a 21-day field safety and effectiveness study, 40 dogs, already well controlled on vetsulin®, were administered vetsulin® using a VetPen® insulin pen loaded with a pre-filled 2.7 mL vetsulin® cartridge and 29 gauge/12 mm pen needles. All dogs enrolled in the study were evaluated for safety. Loss of diabetic control was reported in 10 dogs, 3 of which were withdrawn from the study. Four dogs' loss of control resolved after dose adjustment while still using the insulin pen. For the remaining 3 dogs, the loss of diabetic control was reported at the end of the study and outcome was not documented. Two dogs had injection site reactions: edema in one dog and two instances of crusting in another. Poor appetite and weight loss was reported in one dog.

Cats

In a field effectiveness and safety study, safety data was reported for 78 cats receiving vetsulin®. Hypoglycemia (defined as blood glucose < 50 mg/dL) was reported in 61 cats (88 total incidences). Fifteen of the occurrences (involving 13 cats) were associated with clinical signs described as lethargy, diarrhea, decreased appetite/anorexia, vomiting, and hypothermia. One cat had seizures following accidental overdosing by the owner and again during the subsequent dose adjustment period. The cat responded to supportive therapy and had no further hypoglycemic episodes. In all cases of hypoglycemia, the clinical signs resolved following symptomatic treatment and/or dose adjustment. Polyneuropathy was reported in 4 cats. Two injection site reactions were reported: one as a mildly thickened subcutaneous tissue reaction and the second as a mild bruising.

The following clinical observations occurred in the field study following treatment with vetsulin® and may be directly attributed to the drug or may be secondary to the diabetic state or other underlying conditions in the cats: vomiting, lethargy, diarrhea, decreased appetite/anorexia, pancreatitis, dermal events, respiratory disease, urinary tract disorder, renal disease, dehydration, weight loss, polydipsia, polyuria, behavioral change, and ocular discharge/conjunctivitis. In a smaller field effectiveness and safety study, 14 cats were treated with vetsulin®. Hypoglycemia was reported in 6 cats (8 total occurrences). Lethargy not associated with hypoglycemia was reported in 4 cats (6 total occurrences). The following clinical observations occurred in the field study following treatment with vetsulin® and may be directly attributed to the drug or may be secondary to the diabetic state or other underlying conditions in the cats: foul odor to stool, diarrhea, dull coat, rapid, shallow breathing, stiff gait in rear, gallop rhythm, and pruritus with alopecia.

During the 1998–2007 period, the following adverse events in 50 cats treated with porcine insulin zinc suspension were reported to Intervet International and Intervet Inc.: Death, seizures, lack of effectiveness/dysregulation, hypoglycemia, allergic or skin reaction, lethargy, vomiting/diarrhea, injection pain, hyperthermia, nystagmus, PU/PD, and abnormal behavior.

In a 21-day field safety and effectiveness study, 36 cats, already well controlled on vetsulin®, were administered vetsulin® using a VetPen® insulin pen loaded with a pre-filled 2.7 mL vetsulin® cartridge and 29 gauge/12 mm pen needles. Loss of diabetic control was reported in three cats all of which resolved after dose adjustment while still using the insulin pen. Hypoglycemia was reported in one cat. The cat recovered with supportive care and dose adjustment.

To report suspected adverse drug experiences, call Merck at 1-800-224-5318.

For additional information about adverse drug experience reporting for animal drugs, contact FDA at 1-888-FDA-VETS, or http://www.fda.gov/AnimalVeterinary/SafetyHealth.

GENERAL PHARMACOLOGY

vetsulin® is a mixture of amorphous and crystalline insulin resulting in immediate and prolonged insulin activity. In dogs, vetsulin® may show two peaks of activity. In a laboratory study, 12 healthy adult Beagles were administered vetsulin® at a dose of 0.5 IU/kg. The onset of activity varied from 0.5 to 2 hours; the time to peak activity varied from 1 to 10 hours; and the duration of activity varied from 10 to 24 hours. In diabetic dogs, vetsulin® has two peaks of activity following subcutaneous administration (the first occurs at 2 to 6 hours and the second at 8 to 14 hours). The duration of activity varies between 14 and 24 hours.

In cats, vetsulin® has a single peak of activity. In a laboratory study, 12 healthy adult cats were administered vetsulin® at a dose of 0.5 IU/kg. The onset of activity varied from 0.5 to 2 hours; the time to peak activity varied from 2 to 6 hours; and the duration of activity varied from 8 to 24 hours. In diabetic cats, the peak activity following subcutaneous administration of vetsulin® occurs between 1.5 and 8 hours, and the duration of activity varies between 8 and 12 hours.

The peak(s) of activity, duration of activity, and dose required to adequately control diabetic signs vary between individuals and may vary in the same individual from day to day. The time ranges should only be considered as initial guidelines.

EFFECTIVENESS

Dogs

A total of 66 client-owned dogs were enrolled in and 53 completed the effectiveness and safety field study. The dogs completing the study included 22 breeds of purebred and various mixed breed dogs ranging in age from 4.8 to 14 years, and ranging in weight from 4.2 to 51.3 kg. Of the dogs completing the study, 25 were spayed females and 28 were male (21 neutered and 7 intact).

Dogs were started on vetsulin® at a dose of 1 IU/kg plus a body weight-dependent dose supplement once daily. The initial treatment time to reach acceptable glycemic control (Dose determination period) ranged from 5 to 151 days. Dogs were evaluated for treatment effectiveness three times at 30-day intervals (Study Period). The blood glucose curve means and mean nadirs were compared pre- and post-treatment to assess effectiveness. Glycemic control was considered adequate if an acceptable blood glucose curve was achieved (reduction in hyperglycemia and a nadir of 60 - 160 mg/dL), clinical signs of hyperglycemia (polyuria, polydipsia, and ketonuria) were improved, and hypoglycemia (blood glucose < 50 mg/dL) was avoided. The blood glucose curve mean was reduced from 370 mg/dL pre-treatment to 151 mg/dL, 185 mg/dL, and 184 mg/dL at the three treatment period evaluations. The blood glucose mean nadir was reduced from 315 mg/dL pre-treatment to 93 mg/dL, 120 mg/dL, and 119 mg/dL at the three treatment period evaluations. Sixty days after an adequate vetsulin® dose was initially established, 94%, 96% and 83% of study dogs experienced a reduction in polyuria, polydipsia, and ketonuria, respectively. Investigators reported adequate glycemic control an average of 81% of the time during the Study Period.

In a 21-day field safety and effectiveness study, 40 dogs, already well controlled on vetsulin®, were administered vetsulin® using a VetPen® insulin pen loaded with a pre-filled 2.7 mL vetsulin® cartridge and 29 gauge/12 mm pen needles. Thirty-eight of 40 dogs were evaluated for effectiveness. Thirty-seven of the 38 owners (97.4%) said they were able to learn how to use the pen. Thirty-five of the 38 owners (92.1%) said the pen was well tolerated by the dogs. For 34 of the 38 dogs (89.5%), the investigators said that the diabetes was not negatively affected by the use of the pen.

Cats

A total of 85 client-owned cats (53 males and 25 females—all neutered) of various breeds were enrolled in a 60 day field effectiveness and safety study with continued use up to Day 180. Seven cats were removed from the study prior to the Day 7 evaluation. The remaining cats ranged in age from 3 to 17.5 years and in weight from 1.9 to 10.8 kg. Seventy-two cats completed the study to Day 60 and 66 cats completed to Day 180. The cats were started on vetsulin® at an initial dose of 1 to 2 IU insulin twice daily. Scheduled evaluations occurred at Days 7, 14, 30, 60, and 180. Dose adjustments were allowed at and between the evaluations. Effectiveness was based on blood glucose curve mean, blood glucose nadir and improvement in clinical signs. Blood glucose curve means decreased from 394 mg/dL on Day 0 to 217 mg/dL on Day 60. The mean blood glucose nadir decreased from 343 mg/dL on Day 0 to 146 mg/dL on Day 60. Fourteen client-owned cats (10 males and 4 females—all neutered) of various breeds were enrolled in a 60 day effectiveness and safety field study. The cats ranged in age from 5 to 14 years and in weight from 3.40 to 6.97 kg. Twelve cats completed the study. The cats were started on vetsulin® at an initial dose of 1 to 2 IU insulin twice daily. Scheduled evaluations occurred at Days 7, 14, 30, and 60. Dose adjustments were allowed at and between the evaluations. The blood glucose curve means decreased from 354 mg/dL on Day 0 to 162 mg/dL on Day 60. The mean blood glucose nadir decreased from 321 mg/dL on Day 0 to 99 mg/dL on Day 60. In a 21-day field safety and effectiveness study, 36 cats, already well controlled on vetsulin®, were administered vetsulin® using a VetPen® insulin pen loaded with a pre-filled 2.7 mL vetsulin® cartridge and 29 gauge/12 mm pen needles. Thirty-six owners (100%) said they were able to learn how to use the pen. Thirty-four owners (94.4%) said the pen was well tolerated by the cats. For thirty-five cats (97.2%), the investigators said that the diabetes was not negatively affected by the use of the pen.

HOW SUPPLIED

vetsulin® is supplied as a sterile injectable suspension in multidose vials containing 10 mL of 40 IU/mL porcine insulin zinc suspension or in multidose cartridges containing 2.7 mL of 40 IU/mL porcine insulin zinc suspension. Vials are supplied in cartons of one, 10 mL vial. Cartridges are supplied in cartons of 10, 2.7 mL cartridges.

STORAGE CONDITIONS

Store in an upright position under refrigeration at 2°C to 8°C (36°F to 46°F). Do not freeze. Protect from light. The loaded VetPen® can be stored on its side.

Use contents within 42 days of first puncture.

Additional information about vetsulin®, VetPen®, and diabetes mellitus can be found at www.vetsulin.com
Distributed by Intervet Inc. (d/b/a Merck Animal Health), Rahway, NJ 07065.
Formulated in Germany.
Copyright © 2025 Merck & Co., Inc., Rahway, NJ, USA and its affiliates.
All rights reserved.
Rev. 03/2025

vetsulin® (porcine insulin zinc suspension)

Owner Information Sheet
vetsulin® Injectable Insulin (porcine insulin zinc suspension)
vetsulin® for reduction of hyperglycemia and hyperglycemia-associated
clinical signs in dogs and cats with diabetes mellitus
Generic name: U-40 Purified Porcine Insulin Zinc Suspension

This summary contains important information about vetsulin®. You should read this information before you start giving your pet vetsulin® and review it each time your prescription is refilled. This sheet is provided only as a summary and does not take the place of instructions from your veterinarian. Talk to your veterinarian if you do not understand this information or if you want to know more about vetsulin®.

What is vetsulin®?

vetsulin® is an aqueous suspension of porcine (pork) insulin. Insulin is a hormone produced by the pancreas (a large gland that lies near the stomach). This hormone is necessary for the body's correct use of food, especially sugar.

What is diabetes mellitus?

Diabetes mellitus (DM) occurs when a dog or a cat has inadequate levels of or an abnormal response to insulin. DM is common in middle age and older dogs and cats. Daily insulin injections are usually necessary to treat DM. vetsulin® may help your pet effectively use food, aid in maintaining an acceptable blood sugar (glucose) level, and reduce or eliminate clinical signs commonly seen with DM. Diabetes mellitus may cause some or all of these signs or changes:

- Excessive thirst (Polydipsia)
- Excessive urination (Polyuria)
- Excessive appetite (Polyphagia)
- Weight loss despite good appetite
- Glucose in the urine (Glycosuria)
- Ketones in the urine (Ketonuria)
- Cloudy eyes and vision loss (Diabetic cataracts: dogs)
- Weakness in back legs (Diabetic neuropathy: cats)

Untreated or improperly regulated diabetes may lead to changes in the acidity of the blood (diabetic ketoacidosis) with dehydration, vomiting, weakness, depression, coma, and death.

What kind of results can I expect when my pet is on vetsulin® for DM?

Although vetsulin® is not a cure for DM, it can help control or eliminate many of the complications associated with the disease (such as excessive thirst, urination, and weight loss) and prevent development of life threatening ketoacidosis.

- Response varies from animal to animal but can be quite dramatic.
- In most cases, improvement can be seen within a few days.
- In cats, treatment may lead to diabetes remission (insulin injections no longer required).
- If vetsulin® is discontinued or not given as directed, the signs of diabetes will likely return and life-threatening complications such as ketoacidosis may develop.

Who should not receive vetsulin®?

- Pets known to have a systemic allergy to pork or pork products.
- Pets that have stopped eating or have greatly decreased appetite (anorexia), are vomiting, show signs of extreme drowsiness or fatigue (lethargy) and/or show signs of severe ketoacidosis, should not receive vetsulin® until stabilized with appropriate supportive therapy.
- vetsulin® is for use in animals only. Keep out of reach of children. Seek medical attention immediately if accidental injection occurs.

What to tell/ask your veterinarian before using vetsulin®.

Talk to your veterinarian about:

- The signs of DM you have observed.
- What tests might be done before vetsulin® is prescribed.
- The importance of ovariohysterectomy (spaying), if your dog is an intact female.
- The importance of consistent daily injections, an appropriate and consistent diet, weight control, exercise, and home monitoring of your pet's condition.
- How often your pet may need to be examined by your veterinarian.
- The risks and benefits of using vetsulin®.

Tell your veterinarian if your pet has ever had the following medical problems:

- Side effects when receiving other insulin products
- Digestive upset (vomiting and/or diarrhea)
- Liver disease
- Inflamed pancreas (Pancreatitis)
- Underactive thyroid (Hypothyroidism)
- Overactive thyroid (Hyperthyroidism)
- Cushing's Syndrome (Hyperadrenocorticism)
- Kidney disease

Tell your veterinarian about:

- Any medical problems or allergies that your pet has now or has had.
- All medicines that you are giving or plan to give your pet, including those you can get without a prescription.

What are the possible side effects that may occur during vetsulin® therapy?

The most common side effect experienced with vetsulin® therapy is hypoglycemia (low blood sugar). Hypoglycemia can be caused by:

- Giving too much insulin
- Missing or delaying food
- Change in food, diet, or amount fed
- Change (increase) in exercise
- Infection or illness
- Change in the body's need for insulin
- Diseases of the adrenal, pituitary, or thyroid gland, or progression of liver or kidney disease
- Interaction with other drugs (such as progestogen or glucocorticoids)

Signs of hypoglycemia may occur suddenly and can include:

- Weakness
- Depression
- Behavioral changes
- Muscle twitching

- Anxiety
- Seizures
- Coma
- Death

What do I do in case my pet shows signs of hypoglycemia?

- If your pet is unconscious or having a seizure, this is a medical emergency. Take your pet to your veterinarian immediately.
- If your pet is conscious, rub approximately 1 tablespoon of corn syrup or honey on your pet's gums. When it is able to swallow, give corn syrup or honey by mouth until your pet is alert enough to eat. Feed its usual meal and contact your veterinarian.

Other side effects that can be seen include loss of effectiveness and local or systemic allergic reactions. It is important to contact your veterinarian immediately if you think your pet has a medical problem or side effect from vetsulin® therapy. In particular, please contact your veterinarian if your pet shows any of the following:

- Excessive water consumption for more than 3 days
- Excess urination (including need to urinate at night for a pet that usually sleeps through the night or inappropriate urination in the house)
- Reduced or loss of appetite
- Weakness, seizures, or severe mental depression
- Behavioral change, muscle twitching, or anxiety
- Constipation, vomiting, or diarrhea
- Signs of a bladder infection (small, frequent urinations, straining, blood in the urine)
- Swelling of the head or neck

What else can I do to keep my pet's blood sugar stable?

- Your pet's diet should be consistent and appropriate. A nutritionally complete pet food should be fed in consistent amounts at the same times each day or, at the discretion of your veterinarian, be available continuously.
- "Treats" and changes in diet should generally be avoided unless recommended by your veterinarian.
- Your veterinarian will advise you on how much and when to feed your pet based on the response to vetsulin®.
- Your pet's exercise should remain consistent. Consult with your veterinarian if you expect a major change in activity.
- Develop a schedule with your veterinarian for regular evaluations of your pet's diabetes.

Can vetsulin® be used with other medications?

Progestogen (such as megestrol) and glucocorticoids (such as cortisone, prednisone, dexamethasone, triamcinolone) should be avoided during vetsulin® therapy. Progestogen, glucocorticoids, and certain endocrine diseases may counter the effect of insulin. Other medications may also interfere with your pet's response to insulin. Tell your veterinarian about all the medicines you have given your pet in the past, and any medicines that you are planning to give with vetsulin®. This should include other medicines that you can get without a prescription. Your veterinarian may want to check that all of your pet's medications can be given together.

What do I do in case my pet receives more than the prescribed amount of vetsulin®?

If your pet is given too much vetsulin®, severe (life-threatening) hypoglycemia (low blood sugar) can result. Contact your veterinarian immediately. If your veterinarian is not available, seek other veterinary advice at once. Your pet may need to be hospitalized for observation or treatment.

What do I do if my pet receives less than the prescribed dose, or I miss an injection?

- A missed or inadequate dose may cause temporary recurrence of signs (such as excess thirst and urination) but is not life-threatening.
- Contact your veterinarian as soon as possible for advice on your pet's next dose.
- If you cannot reach your veterinarian and your pet is eating and acting normal, give your pet the usual dose at the next regularly scheduled injection time.

How to give vetsulin® to your pet

Doses of insulin are measured in units. U-40 insulin contains 40 units/mL (1 mL = 1 cc). vetsulin® is available in vials for use with U-40 syringes or in cartridges for use with the VetPen™ injection device. If you are using vials, refer to the section below. If you are using cartridges, refer to the VetPen™ instructions for use provided with the VetPen™.

Use vetsulin® with U-40 syringes only. Use of a syringe other than a U-40 syringe will result in incorrect dosing. A licensed veterinarian must prescribe vetsulin® for your pet, and it should be administered according to your veterinarian's instructions. Your veterinarian will determine the amount of insulin needed (based on the weight of your pet, clinical signs such as water consumption, and laboratory results), instruct you on proper storage and handling, show you how to draw the insulin from the bottle, and instruct you on how to administer the injection. Once you can do this correctly, your veterinarian will provide you with everything you need to care for your pet at home. vetsulin® should be administered with a U-40 insulin syringe according to the following instructions:

Preparing the Dose:

- Wash your hands.
- Remove the vetsulin® bottle from the refrigerator and shake the vial thoroughly until a homogeneous, uniformly milky suspension is obtained. Foam on the surface of the suspension formed during shaking should be allowed to disperse before the product is used and, if required, the product should be gently mixed to maintain a homogeneous, uniformly milky suspension before use. If you see large particles floating in the suspension after thoroughly shaking, do not use the product and contact your veterinarian.
- Carefully remove the cap from the needle.
- Using a U-40 insulin syringe, pull the plunger back to draw air into the syringe to equal the vetsulin® dose.
- Insert the syringe needle into the bottle and inject the air into the bottle.
- Turn the bottle and syringe upside down. Making sure the tip of the needle is in the vetsulin®, withdraw the correct dose into the syringe.
- Before removing the needle from the bottle, check the syringe for any air bubbles. If bubbles are present, hold the syringe straight up and tap its side until the bubbles float to the top. Push them out with the plunger and withdraw the correct dose.
- Remove the needle from the bottle, being careful to not inject yourself.

Giving the injection:

- Injections should be given just under the skin (subcutaneously) 2-5 cm (3/4-2 inches) from the midline of the back (middle of your pet's back running from tail to head), varying from just behind the shoulder blade to slightly in front of the hipbone.
- The injection site should be alternated between your pet's left and right side.
- Using your free hand, pinch up a fold of skin, insert the needle into the center of the fold as instructed by your veterinarian, and push the plunger in as far as it will go.
- Pull the needle out being careful to not inject yourself.
- Dispose of the syringe in an appropriate manner (sharps/biohazard disposal).

How do I store vetsulin®?

vetsulin® should be stored in an upright position under refrigeration 2°C to 8°C (36°F to 46°F). Once loaded with a cartridge, the VetPen™ can be stored on its side under refrigeration.

Do not freeze. Protect from light. Use contents within 42 days of first vial puncture.

What else should I know about vetsulin®?

This sheet provides a summary of information about vetsulin®. If you have any questions or concerns about vetsulin® or DM, talk to your veterinarian.

As with all prescribed medicines, vetsulin® should only be given to the pet for which it was prescribed and for the condition for which it was prescribed.

It is important that your veterinarian periodically evaluate your pet's response to vetsulin® at regular checkups that include blood glucose monitoring. Your veterinarian will best determine if your pet is responding as expected.

Additional information about vetsulin® and DM can be found at www.vetsulin.com

Distributed by Intervet Inc. (d/b/a Merck Animal Health), Rahway, NJ 07065.
Formulated in Germany.

126 E. Lincoln Avenue, Rahway, NJ 07065 • Customer Service 1-800-521-5767
Copyright © 2025 Merck & Co., Inc., Rahway, NJ USA, and its affiliates. All rights reserved.
Rev. 03/2025

PRINCIPAL DISPLAY PANEL - 10 mL Vial Carton

vetsulin®
(porcine insulin zinc
suspension)

40 units per mL (U-40)

For subcutaneous injection
in dogs and cats only.

CAUTION: Federal law restricts this drug to
use by or on the order of a licensed veterinarian.

Approved by FDA under NADA # 141-236

Net contents: 10 mL

MERCK
Animal Health